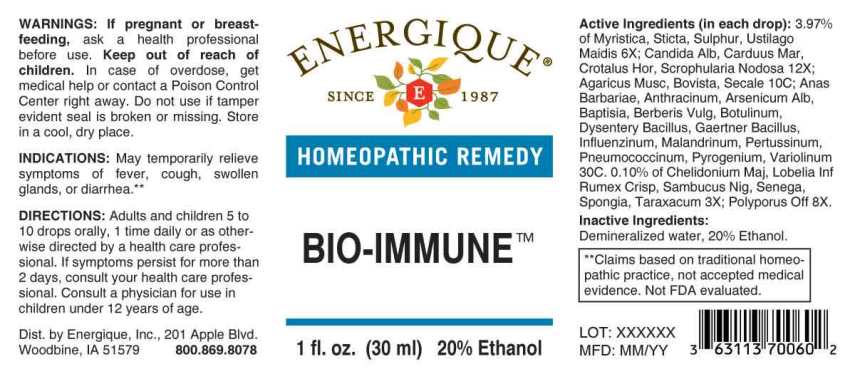 DRUG LABEL: Bio-Immune
NDC: 44911-0653 | Form: LIQUID
Manufacturer: Energique, Inc.
Category: homeopathic | Type: HUMAN OTC DRUG LABEL
Date: 20251006

ACTIVE INGREDIENTS: CHELIDONIUM MAJUS WHOLE 3 [hp_X]/1 mL; LOBELIA INFLATA WHOLE 3 [hp_X]/1 mL; RUMEX CRISPUS ROOT 3 [hp_X]/1 mL; SAMBUCUS NIGRA FLOWERING TOP 3 [hp_X]/1 mL; POLYGALA SENEGA ROOT 3 [hp_X]/1 mL; SPONGIA OFFICINALIS SKELETON, ROASTED 3 [hp_X]/1 mL; TARAXACUM OFFICINALE 3 [hp_X]/1 mL; VIROLA SEBIFERA RESIN 6 [hp_X]/1 mL; LOBARIA PULMONARIA 6 [hp_X]/1 mL; SULFUR 6 [hp_X]/1 mL; USTILAGO MAYDIS 6 [hp_X]/1 mL; LARICIFOMES OFFICINALIS FRUITING BODY 8 [hp_X]/1 mL; CANDIDA ALBICANS 12 [hp_X]/1 mL; MILK THISTLE 12 [hp_X]/1 mL; CROTALUS HORRIDUS HORRIDUS VENOM 12 [hp_X]/1 mL; SCROPHULARIA NODOSA WHOLE 12 [hp_X]/1 mL; AMANITA MUSCARIA FRUITING BODY 10 [hp_C]/1 mL; LYCOPERDON UTRIFORME FRUITING BODY 10 [hp_C]/1 mL; CLAVICEPS PURPUREA SCLEROTIUM 10 [hp_C]/1 mL; CAIRINA MOSCHATA HEART/LIVER AUTOLYSATE 30 [hp_C]/1 mL; BACILLUS ANTHRACIS IMMUNOSERUM RABBIT 30 [hp_C]/1 mL; ARSENIC TRIOXIDE 30 [hp_C]/1 mL; BAPTISIA TINCTORIA ROOT 30 [hp_C]/1 mL; BERBERIS VULGARIS ROOT BARK 30 [hp_C]/1 mL; CLOSTRIDIUM BOTULINUM 30 [hp_C]/1 mL; SHIGELLA DYSENTERIAE 30 [hp_C]/1 mL; SALMONELLA ENTERICA SUBSP. ENTERICA SEROVAR ENTERITIDIS 30 [hp_C]/1 mL; INFLUENZA A VIRUS A/VICTORIA/2570/2019 IVR-215 (H1N1) ANTIGEN (FORMALDEHYDE INACTIVATED) 30 [hp_C]/1 mL; INFLUENZA A VIRUS A/TASMANIA/503/2020 IVR-221 (H3N2) ANTIGEN (FORMALDEHYDE INACTIVATED) 30 [hp_C]/1 mL; INFLUENZA B VIRUS B/WASHINGTON/02/2019 ANTIGEN (FORMALDEHYDE INACTIVATED) 30 [hp_C]/1 mL; INFLUENZA B VIRUS B/PHUKET/3073/2013 ANTIGEN (FORMALDEHYDE INACTIVATED) 30 [hp_C]/1 mL; VACCINIA VIRUS 30 [hp_C]/1 mL; HUMAN SPUTUM, BORDETELLA PERTUSSIS INFECTED 30 [hp_C]/1 mL; STREPTOCOCCUS PNEUMONIAE 30 [hp_C]/1 mL; RANCID BEEF 30 [hp_C]/1 mL; VACCINIA VIRUS STRAIN NEW YORK CITY BOARD OF HEALTH LIVE ANTIGEN 30 [hp_C]/1 mL
INACTIVE INGREDIENTS: WATER; ALCOHOL

DRUG FACTS:

ACTIVE INGREDIENTS:

(in each drop) 3.97% of Myristica Sebifera 6X, Sticta Pulmonaria 6X, Sulphur 6X, Ustilago Maidis 6X; Candida Albicans 12X, Carduus Marianus 12X, Crotalus Horridus 12X, Scrophularia Nodosa 12X; Agaricus Muscarius 10C, Bovista 10C, Secale Cornutum 10C; Anas Barbariae, Hepatis ET Cordis Extractum 30C, Anthracinum 30C, Arsenicum Album 30C, Baptisia Tinctoria 30C, Berberis Vulgaris 30C, Botulinum 30C, Dysentery Bacillus 30C, Gaertner Bacillus (Bach) 30C, Influenzinum (2021-2022) 30C, Malandrinum 30C, Pertussinum 30C, Pneumococcinum 30C, Pyrogenium 30C, Variolinum 30C. 0.10% of Chelidonium Majus 3X, Lobelia Inflata 3X, Rumex Crispus 3X, Sambucus Nigra 3X, Senega Officinalis 3X, Spongia Tosta 3X, Taraxacum Officinale 3X; Polyporus Officinalis 8X.

INDICATIONS:

May temporarily relieve symptoms of fever, cough, swollen glands, or diarrhea.**

**Claims based on traditional homeopathic practice, not accepted medical evidence. Not FDA evaluated.

WARNINGS:

If pregnant or breastfeeding, ask a health professional before use.

Keep out of reach of children. In case of overdose, get medical help or contact a Poison Control Center right away.

Do not use if tamper evident seal is broken or missing.

Store in a cool, dry place.

Keep out of reach of children. In case of overdose, get medical help or contact a Poison Control Center right away.

DIRECTIONS:

Adults and children 5 to 10 drops orally, 1 time daily or as otherwise directed by a health care professional. If symptoms persist for more than 2 days, consult your health care professional. Consult a physician for use in children under 12 years of age.

INDICATIONS:

May temporarily relieve symptoms of fever, cough, swollen glands, or diarrhea.**

**Claims based on traditional homeopathic practice, not accepted medical evidence. Not FDA evaluated.

INACTIVE INGREDIENTS:

Demineralized water, 20% Ethanol.

QUESTIONS:

Dist. by Energique, Inc., 201 Apple Blvd.
Woodbine, IA 51579 800.869.8078

PACKAGE LABEL DISPLAY:

ENERGIQUE

SINCE 1987

HOMEOPATHIC REMEDY

BIO-IMMUNE

1 fl. oz. (30 ml)